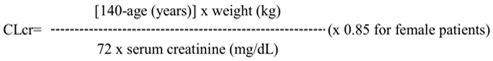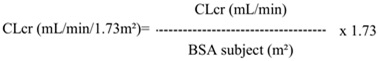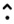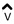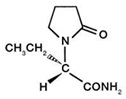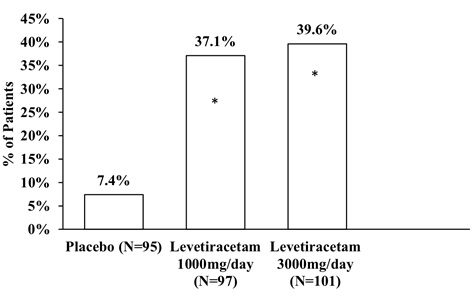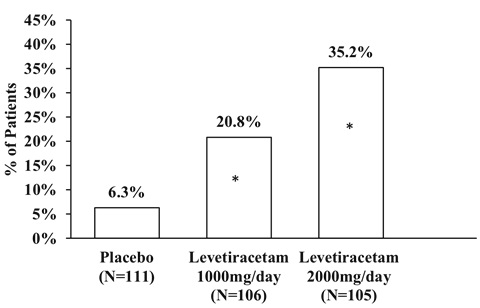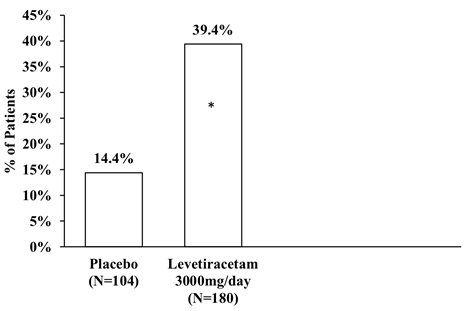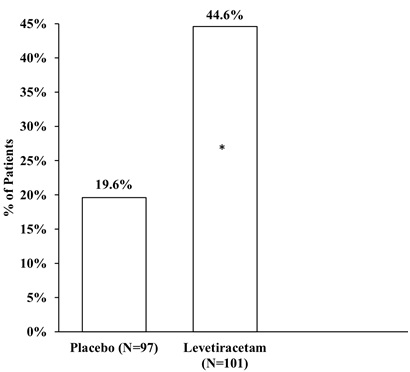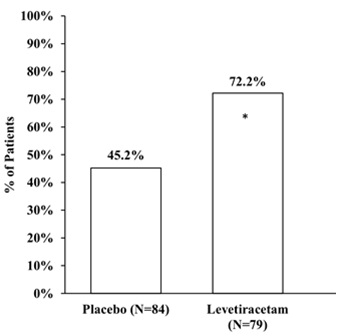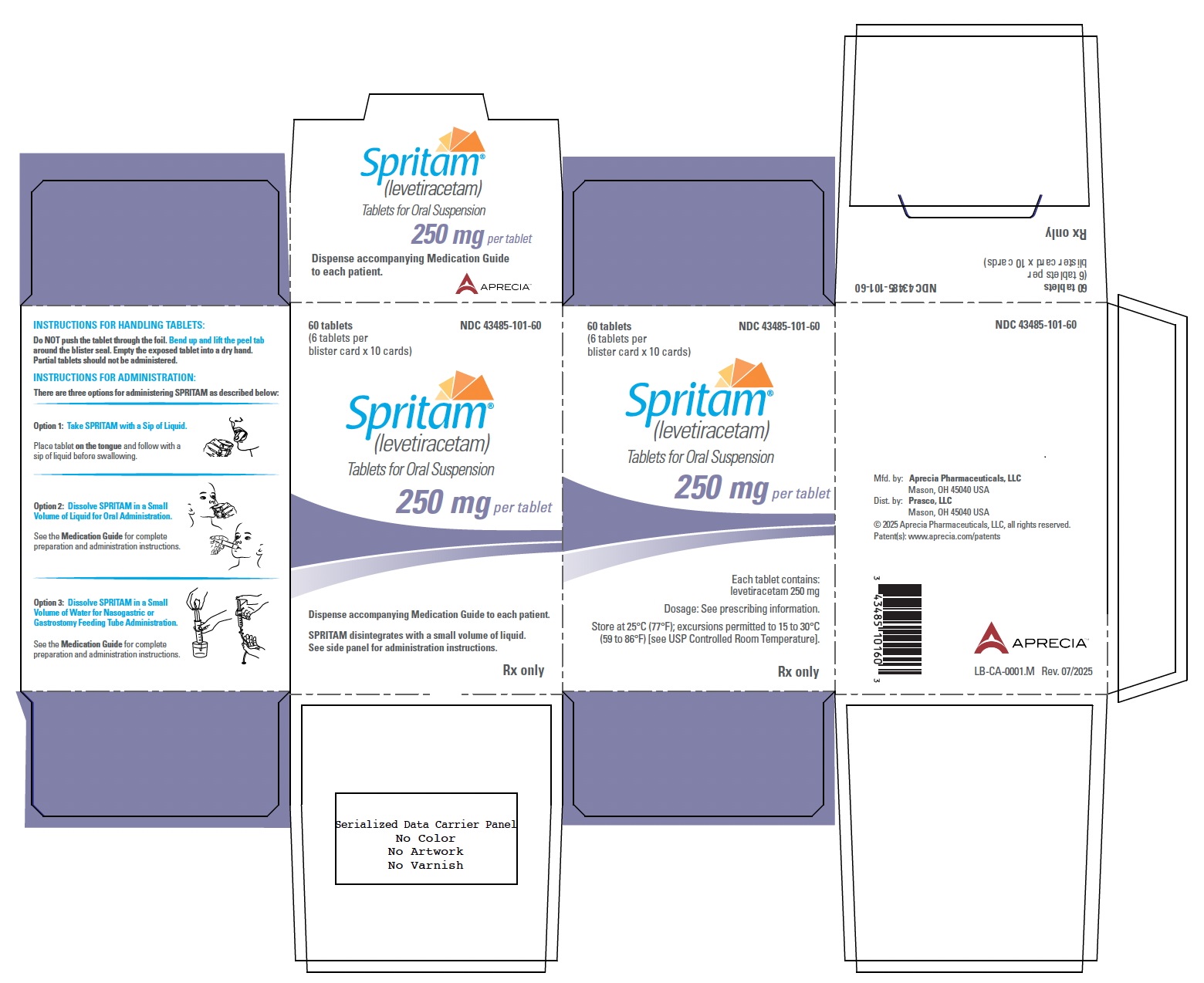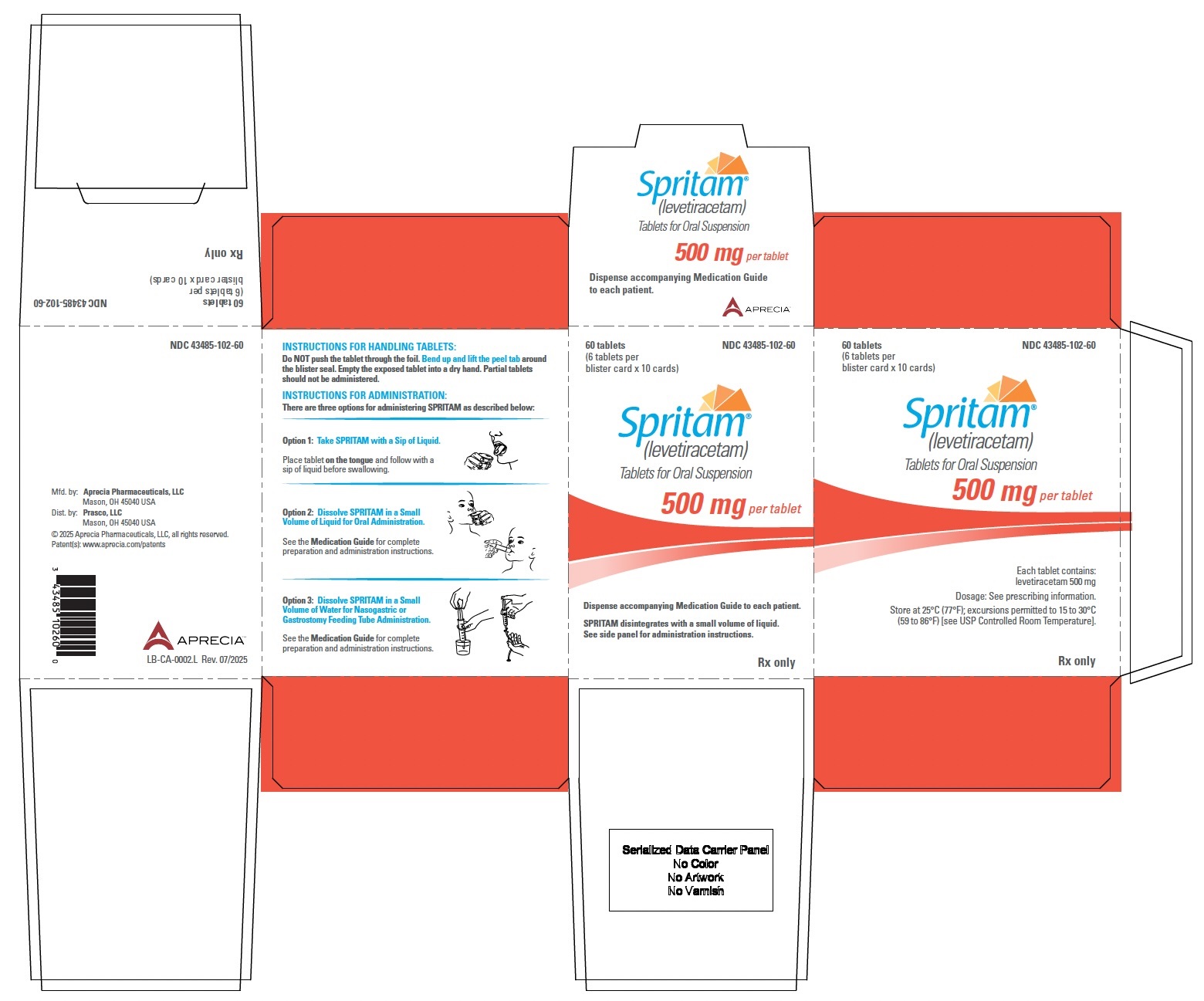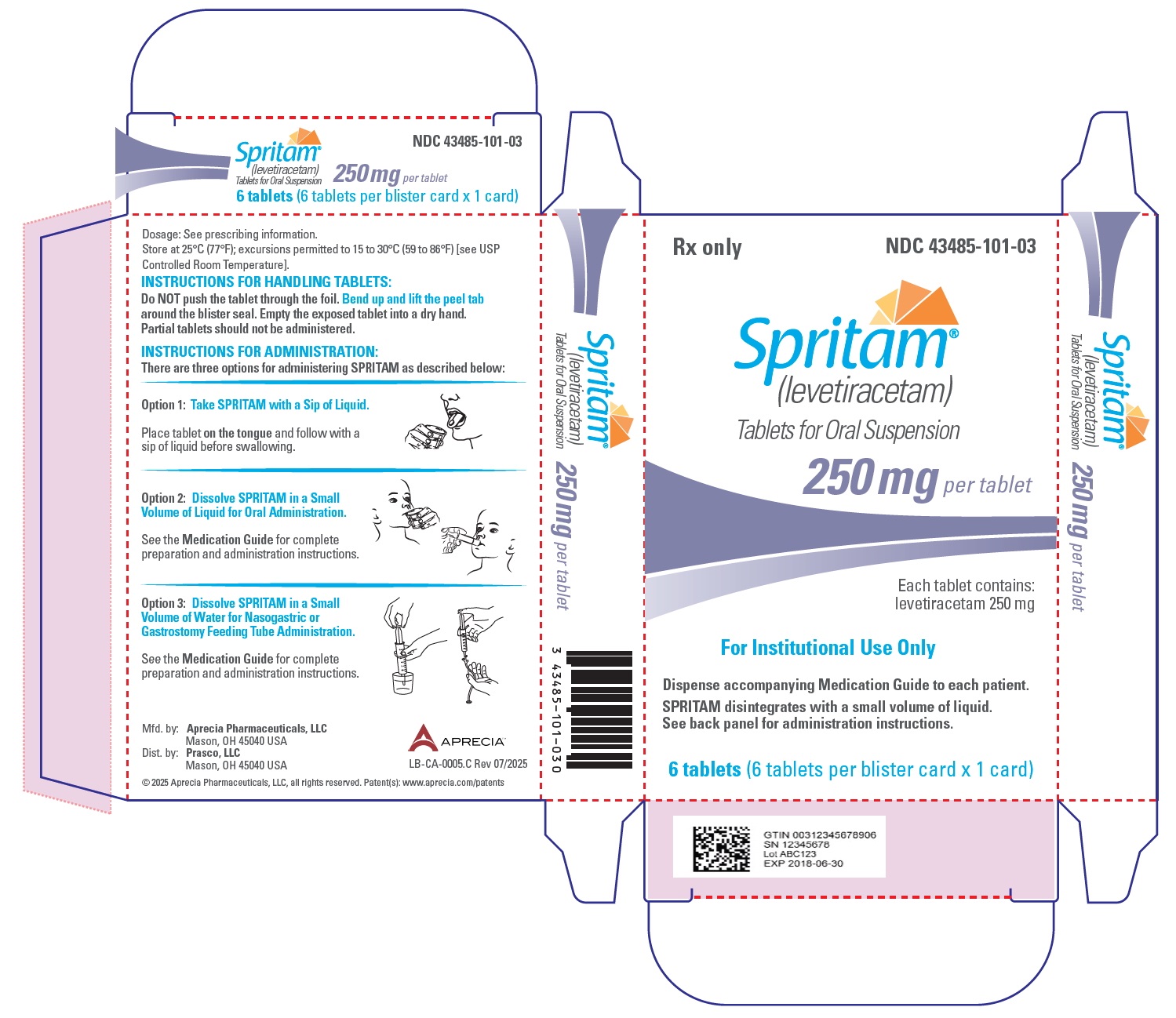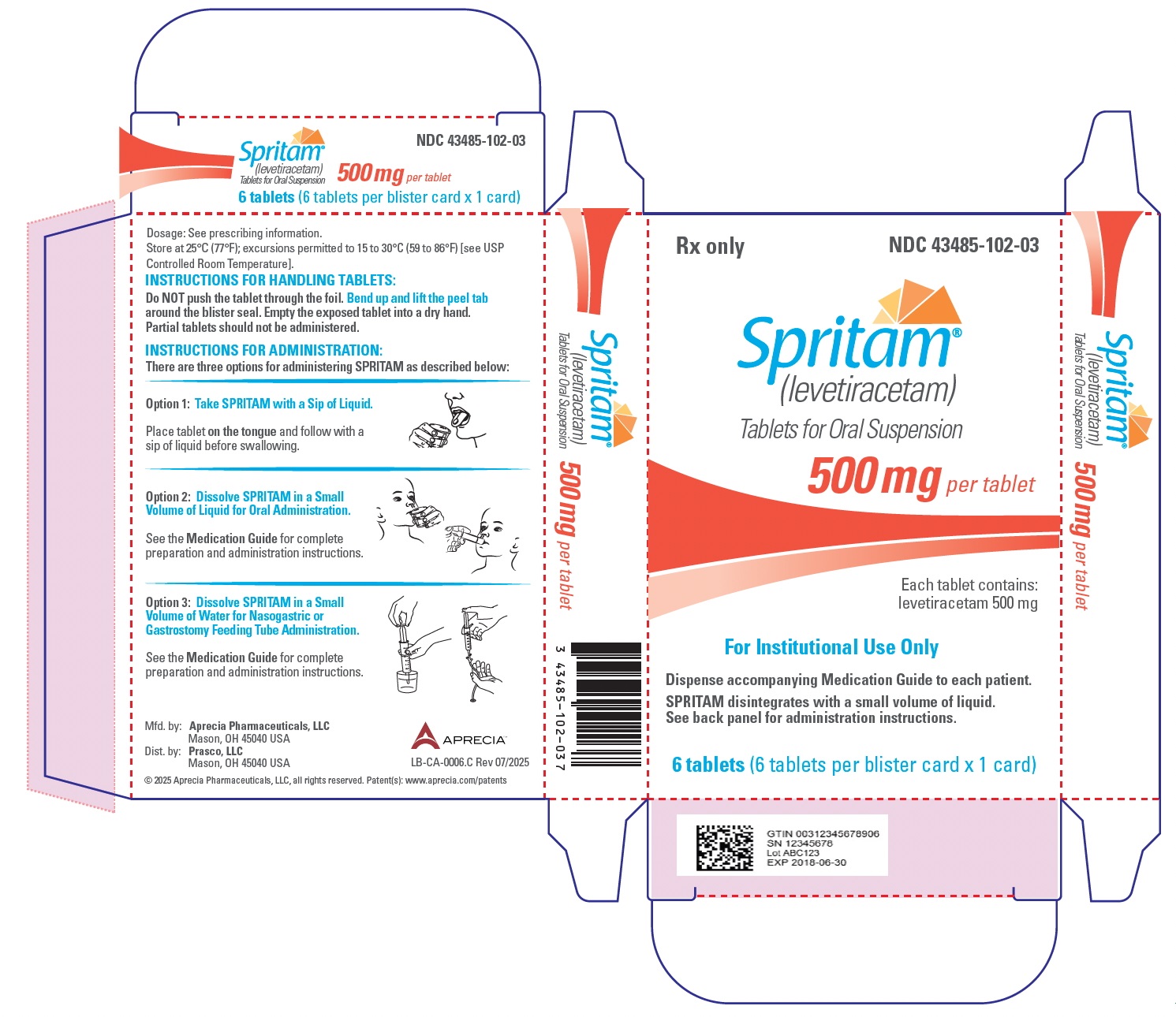 DRUG LABEL: Spritam
NDC: 43485-101 | Form: TABLET, FOR SUSPENSION
Manufacturer: Aprecia Pharmaceuticals, LLC
Category: prescription | Type: HUMAN PRESCRIPTION DRUG LABEL
Date: 20251013

ACTIVE INGREDIENTS: LEVETIRACETAM 250 mg/1 1
INACTIVE INGREDIENTS: SILICON DIOXIDE; GLYCERIN; MANNITOL; CELLULOSE, MICROCRYSTALLINE; POLYSORBATE 20; POVIDONE, UNSPECIFIED; SUCRALOSE; BUTYLATED HYDROXYANISOLE; SPEARMINT

HIGHLIGHTS OF PRESCRIBING INFORMATION

These highlights do not include all the information needed to use SPRITAM® safely and effectively. See full prescribing information for SPRITAM.
SPRITAM (levetiracetam) tablets, for oral suspension
Initial U.S. Approval: 1999

RECENT MAJOR CHANGES

Dosage and Administration (2.1) | 6/2025

1 INDICATIONS AND USAGE

SPRITAM is indicated for the treatment of partial-onset seizures in patients 4 years of age and older weighing more than 20 kg (1.1)

SPRITAM is indicated for adjunctive therapy for the treatment of:

- Myoclonic seizures in patients 12 years of age and older with juvenile myoclonic epilepsy (1.2)
- Primary generalized tonic-clonic seizures in patients 6 years of age and older with idiopathic generalized epilepsy (1.3)

2 DOSAGE AND ADMINISTRATION

- SPRITAM is intended to disintegrate in the mouth when taken with a sip of liquid. Swallow only after the tablet disintegrates. Do not swallow tablet(s) intact. Partial tablet(s) should not be administered (2.1)
- Alternately, add whole SPRITAM tablet(s) to a small volume of liquid in a cup (one tablespoon or enough to cover the medicine). Allow the tablet(s) to disperse prior to consuming entire contents immediately (2.1)

- SPRITAM may also be administered via nasogastric or gastrostomy feeding tubes (2.1)
- Recommended dosage (2.2):
  Age and Body Weight | Initial Dosage | Titration Regimen | Maximum or Recommended Dosage
  Adults and pediatric patients weighing over 40 kg | 500 mg twice daily | Increase by 500 mg twice daily every 2 weeks | Partial-Onset Seizures Maximum dosage of 1,500 mg twice daily Myoclonic± and PGTC± Recommended dosage of 1,500 mg twice daily
  Pediatric patients weighing 20 kg to 40 kg | 250 mg twice daily | Increase by 250 mg twice daily every 2 weeks | Maximum 750 mg twice daily

Adult Patients with Renal Impairment

- Dose adjustment is recommended based on creatinine clearance (2.3, 8.6)

3 DOSAGE FORMS AND STRENGTHS

- Tablets for oral suspension: 250 mg and 500 mg (3)

4 CONTRAINDICATIONS

- Known hypersensitivity to levetiracetam; angioedema and anaphylaxis have occurred (4, 5.4)

5 WARNINGS AND PRECAUTIONS

- Behavioral Abnormalities: Psychotic symptoms, irritability, and aggressive behavior have been observed: Monitor for signs and symptoms (5.1)
- Suicidal Behavior and Ideation: Monitor for new or worsening depression, suicidal thoughts/behavior, and/or changes in mood or behavior (5.2)
- Monitor for somnolence and fatigue and advise patients not to drive or operate machinery until they have gained experience on SPRITAM (5.3)
- Serious Dermatological Reactions: Discontinue SPRITAM at the first sign of rash unless clearly not drug related (5.5)
- Drug Reaction with Eosinophilia and Systemic Symptoms / Multiorgan Hypersensitivity: Discontinue if no alternative etiology (5.6)
- Coordination Difficulties: Monitor for ataxia, abnormal gait, and incoordination. Advise patients to not drive or operate machinery until they have gained experience on SPRITAM (5.7)
- Withdrawal Seizures: SPRITAM must be gradually withdrawn (5.8)

6 ADVERSE REACTIONS

Most common adverse reactions (incidence ≥ 5% more than placebo) include:

- Adults: somnolence, asthenia, infection, and dizziness (6.1)
- Pediatrics: fatigue, aggression, nasal congestion, decreased appetite, and irritability (6.1)

To report SUSPECTED ADVERSE REACTIONS, contact Aprecia Pharmaceuticals, LLC at 1-844-882-7732 or FDA at 1-800-FDA-1088 or www.fda.gov/medwatch.

8 USE IN SPECIFIC POPULATIONS

- Pregnancy: Plasma levels of levetiracetam may be decreased and therefore need to be monitored closely during pregnancy; based on animal data, may cause fetal harm (5.11, 8.1)

FULL PRESCRIBING INFORMATION

1 INDICATIONS AND USAGE

1.1 Partial-Onset Seizures

SPRITAM is indicated for the treatment of partial-onset seizures in patients 4 years of age and older weighing more than 20 kg.

1.2 Myoclonic Seizures in Patients with Juvenile Myoclonic Epilepsy

SPRITAM is indicated as adjunctive therapy for the treatment of myoclonic seizures in patients 12 years of age and older with juvenile myoclonic epilepsy.

1.3 Primary Generalized Tonic-Clonic Seizures

SPRITAM is indicated as adjunctive therapy for the treatment of primary generalized tonic‑clonic seizures in patients 6 years of age and older with idiopathic generalized epilepsy.

2 DOSAGE AND ADMINISTRATION

2.1 Important Preparation and Administration Instructions

The SPRITAM dosing regimen depends on the indication, age group, and renal function. Administer SPRITAM with or without food. Do not administer partial tablets.

Patients should be instructed not to push the tablet through the foil. The foil should be peeled away from the blister by bending up and lifting the peel tab around the blister seal.

Oral Administration

SPRITAM is intended to disintegrate in the mouth when taken with a sip of liquid, one tablet at a time. As a primary method of administration, place one tablet on the tongue with a dry hand, follow with a sip of liquid and swallow only after the tablet disintegrates. Repeat this step, if needed, until the full dose has been administered. Do not swallow tablet(s) intact. SPRITAM disintegrates in a mean time of 11 seconds (ranging from 2 to 27 seconds) in the mouth when taken with a sip of liquid.

Alternately, add whole SPRITAM tablet(s) to a small volume of liquid in a cup (one tablespoon or enough liquid to cover the medicine). Allow the tablet(s) to fully disperse, then immediately consume the entire contents by mouth using the cup or an oral syringe. After administration of the suspension, re-suspend any residue by adding an additional small volume of liquid to the cup, swirl, then swallow the entire contents.

Nasogastric Tube (NG Tube) or Gastrostomy Tube (G-Tube) Administration

For patients who have a NG tube or G tube (French size 10 to 14) in place, administer SPRITAM as follows:

- Place the number of whole tablets needed for the prescribed dose in a small dosing cup,
- Add approximately 10 mL of room temperature water.
- Gently swirl the cup until the tablet(s) disperse.
- Draw up the mixture into a 10 mL oral catheter-tip syringe, hold the syringe in a vertical position, and administer immediately via feeding tube.
- After administration, flush the feeding tube twice, as follows:
  - Add another 10 mL of room temperature water to the dosing cup that contained the dispersion.
  - Swirl the cup to re-suspend any tablet residue.
  - Draw up the mixture into the same oral syringe and immediately push through the feeding tube.

2.2 Recommended Dosage

See Table 1 for the recommended dosage for patients with partial-onset seizures, myoclonic seizures with juvenile myoclonic epilepsy, and primary generalized tonic-clonic seizures.

Table 1: Recommended Dosage for Patients with:
Partial-Onset Seizures (4 years age and older)*,
Myoclonic Seizures (12 years of age and older), and
Primary Generalized Tonic-Clonic Seizures (PGTC) (6 years of age and older)

Age and Body Weight | Initial Dosage | Titration Regimen | Maximum or Recommended Dosage
Adults and pediatric patients weighing over 40 kg | 500 mg twice daily (1,000 mg daily) | Increase by 500 mg twice daily (1,000 mg daily) every 2 weeks | Partial-Onset Seizures** Maximum dosage of 1,500 mg twice daily (3,000 mg daily)** Myoclonic± and PGTC± Recommended dosage of 1,500 mg twice daily (3,000 mg daily)
Pediatric patients weighing 20 kg to 40 kg | 250 mg twice daily (500 mg daily) | Increase by 250 mg twice daily (500 mg daily) every 2 weeks | Maximum dosage of 750 mg twice daily (1,500 mg daily)
* The recommended dosing for monotherapy and adjunctive therapy is the same.
** There is no evidence that doses greater than 3,000 mg daily confer additional benefit.
± The effectiveness of doses lower than 3,000 mg daily has not been adequately studied.

2.3 Dosage Adjustments in Adult Patients with Renal Impairment

SPRITAM dosing must be individualized according to the patient's renal function status. Recommended dosage adjustments for adults are shown in Table 2. In order to calculate the dose recommended for patients with renal impairment, creatinine clearance adjusted for body surface area must be calculated. To do this an estimate of the patient's creatinine clearance (CLcr) in mL/min must first be calculated using the following formula:

Then CLcr is adjusted for body surface area (BSA) as follows:

Table 2: Dosing Regimen For Adult Patients With Renal Impairment
Group | Creatinine Clearance (mL/min/1.73m^2) | SPRITAM Dosage (mg) | Frequency
Normal | >80 | 500 to 1,500 | Every 12 hours
Mild | 50-80 | 500 to 1,000 | Every 12 hours
Moderate | 30-50 | 250 to 750 | Every 12 hours
Severe | <30 | 250 to 500 | Every 12 hours
ESRD patients using dialysis | — | 500 to 1,000^1 | Every 24 hours^1
^1 Following dialysis, a 250 to 500 mg supplemental dose is recommended.

2.4 Discontinuation of SPRITAM

Avoid abrupt withdrawal of SPRITAM in order to reduce the risk of increased seizure frequency and status epilepticus [see Warnings and Precautions (5.8)].

3 DOSAGE FORMS AND STRENGTHS

Tablet(s) for oral suspension:

- 250 mg: round, white to off-white, spearmint-flavored, marked with "" on one side
- 500 mg: round, white to off-white, spearmint-flavored, marked with "" on one side

4 CONTRAINDICATIONS

SPRITAM is contraindicated in patients with a hypersensitivity to levetiracetam. Reactions have included anaphylaxis and angioedema [see Warnings and Precautions (5.4)].

5 WARNINGS AND PRECAUTIONS

5.1 Behavioral Abnormalities and Psychotic Symptoms

SPRITAM may cause behavioral abnormalities and psychotic symptoms. Patients treated with SPRITAM should be monitored for psychiatric signs and symptoms.

Behavioral abnormalities

In clinical studies, 13% of adult levetiracetam-treated patients and 38% of pediatric levetiracetam-treated patients (4 to 16 years of age), compared to 6% and 19% of adult and pediatric placebo-treated patients, respectively, experienced non-psychotic behavioral symptoms (reported as aggression, agitation, anger, anxiety, apathy, depersonalization, depression, emotional lability, hostility, hyperkinesias, irritability, nervousness, neurosis, and personality disorder).

A randomized double-blind, placebo-controlled study was performed to assess the neurocognitive and behavioral effects of levetiracetam as adjunctive therapy in pediatric patients (4 to 16 years of age). The results from an exploratory analysis indicated a worsening in levetiracetam-treated patients on aggressive behavior (one of eight behavior dimensions) as measured in a standardized and systematic way using a validated instrument, the Achenbach Child Behavior Checklist (CBCL/6-18).

In clinical studies in pediatric patients 1 month to < 4 years of age, irritability was reported in 12% of the levetiracetam-treated patients compared to 0% of placebo-treated patients.

In clinical studies, 1.7% of adult levetiracetam-treated patients discontinued treatment due to behavioral adverse reactions, compared to 0.2% of placebo-treated patients. The treatment dose was reduced in 0.8% of adult levetiracetam-treated patients and in 0.5% of placebo-treated patients. Overall, 11% of levetiracetam-treated pediatric patients experienced behavioral symptoms associated with discontinuation or dose reduction, compared to 6% of placebo-treated patients.

Psychotic symptoms

In clinical studies, 1% of levetiracetam-treated adult patients, 2% of levetiracetam-treated pediatric patients 4 to 16 years of age, and 17% of levetiracetam-treated pediatric patients 1 month to < 4 years of age experienced psychotic symptoms, compared to 0.2%, 2%, and 5% in the corresponding age groups treated with placebo. In the controlled study that assessed the neurocognitive and behavioral effects of levetiracetam in pediatric patients 4 to 16 years of age, 1.6% of levetiracetam-treated patients experienced paranoia, compared to 0% of placebo-treated patients. In the same study, 3.1% of levetiracetam-treated patients experienced confusional state, compared to 0% of placebo-treated patients [see Use in Specific Populations (8.4)].

In clinical studies, two (0.3%) levetiracetam-treated adult patients were hospitalized and their treatment was discontinued due to psychosis. Both events, reported as psychosis, developed within the first week of treatment and resolved within 1 to 2 weeks following treatment discontinuation. There was no difference between drug and placebo‑treated patients in the incidence of the pediatric patients who discontinued treatment due to psychotic and non-psychotic adverse reactions.

5.2 Suicidal Behavior and Ideation

Antiepileptic drugs (AEDs), including SPRITAM, increase the risk of suicidal thoughts or behavior in patients taking these drugs for any indication. Patients treated with any AED for any indication should be monitored for the emergence or worsening of depression, suicidal thoughts or behavior, and/or any unusual changes in mood or behavior.

Pooled analyses of 199 placebo-controlled clinical trials (mono- and adjunctive therapy) of 11 different AEDs showed that patients randomized to one of the AEDs had approximately twice the risk (adjusted Relative Risk 1.8, 95% CI:1.2, 2.7) of suicidal thinking or behavior compared to patients randomized to placebo. In these trials, which had a median treatment duration of 12 weeks, the estimated incidence rate of suicidal behavior or ideation among 27,863 AED-treated patients was 0.43%, compared to 0.24% among 16,029 placebo-treated patients, representing an increase of approximately one case of suicidal thinking or behavior for every 530 patients treated. There were four suicides in drug-treated patients in the trials and none in placebo-treated patients, but the number is too small to allow any conclusion about drug effect on suicide.

The increased risk of suicidal thoughts or behavior with AEDs was observed as early as one week after starting drug treatment with AEDs and persisted for the duration of treatment assessed. Because most trials included in the analysis did not extend beyond 24 weeks, the risk of suicidal thoughts or behavior beyond 24 weeks could not be assessed.

The risk of suicidal thoughts or behavior was generally consistent among drugs in the data analyzed. The finding of increased risk with AEDs of varying mechanisms of action and across a range of indications suggests that the risk applies to all AEDs used for any indication. The risk did not vary substantially by age (5-100 years) in the clinical trials analyzed. Table 3 shows absolute and relative risk by indication for all evaluated AEDs.

Table 3: Risk by Indication for Antiepileptic Drugs in the Pooled Analysis
Indication | Placebo Patients with Events Per 1000 Patients | Drug Patients with Events Per 1000 Patients | Relative Risk: Incidence of Events in Drug Patients/ Incidence in Placebo Patients | Risk Difference: Additional Drug Patients with Events Per 1000 Patients
Epilepsy | 1.0 | 3.4 | 3.5 | 2.4
Psychiatric | 5.7 | 8.5 | 1.5 | 2.9
Other | 1.0 | 1.8 | 1.9 | 0.9
Total | 2.4 | 4.3 | 1.8 | 1.9

The relative risk for suicidal thoughts or behavior was higher in clinical trials for epilepsy than in clinical trials for psychiatric or other conditions, but the absolute risk differences were similar for the epilepsy and psychiatric indications.

Anyone considering prescribing SPRITAM or any other AED must balance the risk of suicidal thoughts or behaviors with the risk of untreated illness. Epilepsy and many other illnesses for which AEDs are prescribed are themselves associated with morbidity and mortality and an increased risk of suicidal thoughts and behavior. Should suicidal thoughts and behavior emerge during treatment, the prescriber needs to consider whether the emergence of these symptoms in any given patient may be related to the illness being treated.

5.3 Somnolence and Fatigue

SPRITAM may cause somnolence and fatigue. Patients should be monitored for these signs and symptoms and advised not to drive or operate machinery until they have gained sufficient experience on SPRITAM to gauge whether it adversely affects their ability to drive or operate machinery.

Somnolence

In controlled trials of adult patients with epilepsy experiencing partial-onset seizures, 15% of levetiracetam-treated patients reported somnolence, compared to 8% of placebo-treated patients. There was no clear dose response up to 3000 mg/day. In a study where there was no titration, about 45% of patients receiving 4000 mg/day reported somnolence. The somnolence was considered serious in 0.3% of levetiracetam-treated patients, compared to 0% in the placebo group. About 3% of levetiracetam-treated patients discontinued treatment due to somnolence, compared to 0.7% of placebo-treated patients. In 1.4% of levetiracetam-treated patients and 0.9% of placebo-treated patients, the dose was reduced, while 0.3% of the levetiracetam-treated patients were hospitalized due to somnolence.

Asthenia

In controlled trials of adult patients with epilepsy experiencing partial-onset seizures, 15% of levetiracetam-treated patients reported asthenia, compared to 9% of placebo-treated patients. Treatment was discontinued due to asthenia in 0.8% of levetiracetam-treated patients as compared to 0.5% of placebo-treated patients. In 0.5% of levetiracetam-treated patients and in 0.2% of placebo-treated patients, the dose was reduced due to asthenia.

Somnolence and asthenia occurred most frequently within the first 4 weeks of treatment. In general, the incidences of somnolence and fatigue in the pediatric partial-onset seizure studies, and in pediatric and adult myoclonic and primary generalized tonic-clonic studies were comparable to those of the adult partial-onset seizure studies.

5.4 Anaphylaxis and Angioedema

SPRITAM can cause anaphylaxis or angioedema after the first dose or at any time during treatment. Signs and symptoms in cases reported in the postmarketing setting with levetiracetam have included hypotension, hives, rash, respiratory distress, and swelling of the face, lip, mouth, eye, tongue, throat, and feet. In some reported cases, reactions were life-threatening and required emergency treatment. If a patient develops signs or symptoms of anaphylaxis or angioedema, SPRITAM should be discontinued and the patient should seek immediate medical attention. SPRITAM should be discontinued permanently if a clear alternative etiology for the reaction cannot be established [see Contraindications (4)].

5.5 Serious Dermatological Reactions

Serious dermatological reactions, including Stevens-Johnson syndrome (SJS) and toxic epidermal necrolysis (TEN), have been reported in both pediatric and adult patients treated with levetiracetam. The median time of onset is reported to be 14 to 17 days, but cases have been reported at least four months after initiation of treatment. Recurrence of the serious skin reactions following rechallenge with levetiracetam has also been reported. SPRITAM should be discontinued at the first sign of a rash, unless the rash is clearly not drug-related. If signs or symptoms suggest SJS/TEN, use of this drug should not be resumed and alternative therapy should be considered.

5.6 Drug Reaction with Eosinophilia and Systemic Symptoms (DRESS)/Multiorgan Hypersensitivity

Drug Reaction with Eosinophilia and Systemic Symptoms (DRESS), also known as multiorgan hypersensitivity, has been reported in patients taking antiepileptic drugs, including levetiracetam. These events can be fatal or life-threatening, particularly if diagnosis and treatment do not occur as early as possible. DRESS typically, although not exclusively, presents with fever, rash, lymphadenopathy, and/or facial swelling, in association with other organ system involvement, such as hepatitis, nephritis, hematological abnormalities, myocarditis, or myositis, sometimes resembling an acute viral infection. Eosinophilia is often present. Because this disorder is variable in its expression, other organ systems not noted here may be involved. It is important to note that early manifestations of hypersensitivity, such as fever or lymphadenopathy, may be present even though rash is not evident. If such signs or symptoms are present, the patient should be evaluated immediately. SPRITAM should be discontinued if an alternative etiology for the signs or symptoms cannot be established [see Contraindication (4)].

5.7 Coordination Difficulties

SPRITAM may cause coordination difficulties.

In controlled clinical studies in adult patients with partial-onset seizures, 3.4% of adult levetiracetam-treated patients experienced coordination difficulties (reported as either ataxia, abnormal gait, or incoordination), compared to 1.6% of placebo-treated patients. A total of 0.4% of patients in controlled clinical studies discontinued levetiracetam treatment due to ataxia, compared to 0% of placebo-treated patients. In 0.7% of levetiracetam-treated patients and in 0.2% of placebo-treated patients, the dose was reduced due to coordination difficulties, while one of the levetiracetam-treated patients was hospitalized due to worsening of pre-existing ataxia. These events occurred most frequently within the first 4 weeks of treatment.

Patients should be monitored for these signs and symptoms and advised not to drive or operate machinery until they have gained sufficient experience on SPRITAM to gauge whether it could adversely affect their ability to drive or operate machinery.

5.8 Withdrawal Seizures

As with most antiepileptic drugs, SPRITAM should generally be withdrawn gradually because of the risk of increased seizure frequency and status epilepticus. If withdrawal is needed because of a serious adverse reaction, rapid discontinuation can be considered.

5.9 Hematologic Abnormalities

SPRITAM can cause hematologic abnormalities. Hematologic abnormalities occurred in clinical trials with levetiracetam and included decreases in white blood cell (WBC), neutrophil, and red blood cell (RBC) counts; decreases in hemoglobin and hematocrit; and increases in eosinophil counts. Cases of agranulocytosis, pancytopenia, and thrombocytopenia have been reported in the postmarketing setting. A complete blood count is recommended in patients experiencing significant weakness, pyrexia, recurrent infections, or coagulation disorders.

Partial-Onset Seizures

Adults

Minor, but statistically significant decreases compared to placebo, in total mean RBC count (0.03 x 10^6/mm^3), mean hemoglobin (0.09 g/dL), and mean hematocrit (0.38%), were seen in levetiracetam-treated patients in controlled trials.

A total of 3.2% of levetiracetam‑treated and 1.8% of placebo‑treated patients had at least one possibly significant (≤ 2.8 × 10^9/L) decreased WBC, and 2.4% of levetiracetam‑treated and 1.4% of placebo‑treated patients had at least one possibly significant (≤ 1.0 × 10^9/L) decreased neutrophil count. Of the levetiracetam‑treated patients with a low neutrophil count, all but one rose towards or to baseline with continued treatment. No patient was discontinued secondary to low neutrophil counts.

Pediatric Patients 4 Years to Less Than 16 Years of Age

Statistically significant decreases in WBC and neutrophil counts were seen in levetiracetam‑treated patients as compared to placebo. The mean decreases from baseline in the levetiracetam‑treated group were -0.4 × 10^9/L and -0.3 × 10^9/L, respectively, whereas there were small increases in the placebo group. Mean relative lymphocyte counts increased by 1.7% in levetiracetam‑treated patients, compared to a decrease of 4% in placebo‑treated patients (statistically significant).

In a controlled trial, more levetiracetam-treated patients had a possibly clinically significant abnormally low WBC value (3% of levetiracetam‑treated patients versus 0% of placebo‑treated patients); however, there was no apparent difference between treatment groups with respect to neutrophil count (5% of levetiracetam‑treated patients versus 4.2% of placebo‑treated patients). No patient was discontinued secondary to low WBC or neutrophil counts.

In a controlled cognitive and neuropsychological safety study, 5 patients (8.6%) in the levetiracetam‑treated group and two patients (6.1%) in the placebo‑treated group had high eosinophil count values that were possibly clinically significant (≥ 10% or ≥ 0.7×10^9/L).

5.10 Increase in Blood Pressure

In a randomized, placebo-controlled study in patients 1 month to < 4 years of age, a significantly higher risk of increased diastolic blood pressure was observed in levetiracetam-treated patients (17%), compared to the placebo-treated patients (2%). There was no overall difference in mean diastolic blood pressure between the treatment groups. This disparity between the levetiracetam and placebo treatment groups was not observed in the studies of older pediatric patients or in adults.

Monitor patients 1 month to <4 years of age for increases in diastolic blood pressure.

5.11 Seizure Control During Pregnancy

Physiological changes may gradually decrease plasma levels of levetiracetam throughout pregnancy. This decrease is more pronounced during the third trimester. It is recommended that patients be monitored carefully during pregnancy. Close monitoring should continue through the postpartum period especially if the dose was changed during pregnancy.

6 ADVERSE REACTIONS

The following serious adverse reactions are described below and elsewhere in the labeling:

- Behavioral Abnormalities and Psychotic Symptoms [see Warnings and Precautions (5.1)]
- Suicidal Behavior and Ideation [see Warnings and Precautions (5.2)]
- Somnolence and Fatigue [see Warnings and Precautions (5.3)]
- Anaphylaxis and Angioedema [see Warnings and Precautions (5.4)]
- Serious Dermatological Reactions [see Warnings and Precautions (5.5)]
- Drug Reaction with Eosinophilia and Systemic Symptoms (DRESS)/Multiorgan Hypersensitivity [see Warnings and Precautions (5.6)]
- Coordination Difficulties [see Warnings and Precautions (5.7)]
- Hematologic Abnormalities [see Warnings and Precautions (5.9)]
- Increase in Blood Pressure [see Warnings and Precautions (5.10)]

6.1 Clinical Trials Experience

Because clinical trials are conducted under widely varying conditions, adverse reaction rates observed in the clinical trials of a drug cannot be directly compared to rates in the clinical trials of another drug and may not reflect the rates observed in practice.

Partial-Onset Seizures

Adults

In controlled clinical studies in adults with partial-onset seizures [see Clinical Studies (14.1)], the most common adverse reactions in patients receiving levetiracetam in combination with other AEDs, for events with rates greater than placebo, were somnolence, asthenia, infection, and dizziness. Of the most common adverse reactions in adults experiencing partial-onset seizures, asthenia, somnolence, and dizziness occurred predominantly during the first 4 weeks of treatment with levetiracetam.

Table 4 lists adverse reactions that occurred in at least 1% of adult epilepsy patients receiving levetiracetam in placebo-controlled studies and were numerically more common than in patients treated with placebo. In these studies, either levetiracetam or placebo was added to concurrent AED therapy.

Table 4: Adverse Reactions in Pooled Placebo-Controlled, Adjunctive Studies in Adults with Partial-Onset Seizures
Adverse Reaction | Levetiracetam (N=769) % | Placebo (N=439) %
Asthenia | 15 | 9
Somnolence | 15 | 8
Headache | 14 | 13
Infection | 13 | 8
Dizziness | 9 | 4
Pain | 7 | 6
Pharyngitis | 6 | 4
Depression | 4 | 2
Nervousness | 4 | 2
Rhinitis | 4 | 3
Anorexia | 3 | 2
Ataxia | 3 | 1
Vertigo | 3 | 1
Amnesia | 2 | 1
Anxiety | 2 | 1
Cough Increased | 2 | 1
Diplopia | 2 | 1
Emotional Lability | 2 | 0
Hostility | 2 | 1
Paresthesia | 2 | 1
Sinusitis | 2 | 1

In controlled adult clinical studies, 15% of patients receiving levetiracetam and 12% receiving placebo either discontinued or had a dose reduction as a result of an adverse reaction. Table 5 lists the most common (> 1%) adverse reactions that resulted in discontinuation or dose reduction and that occurred more frequently in levetiracetam-treated patients than in placebo-treated patients.

Table 5: Adverse Reactions that Resulted in Discontinuation or Dose Reduction in Pooled Placebo-Controlled Studies in Adults with Partial-Onset Seizures
Adverse Reaction | Levetiracetam (N=769) % | Placebo (N=439) %
Somnolence | 4 | 2
Dizziness | 1 | 0

Pediatric Patients 4 Years to Less Than 16 Years of Age

The adverse reaction data presented below was obtained from a pooled analysis of two controlled clinical studies in pediatric patients 4 to less than 16 years of age with partial-onset seizures. The most common adverse reactions in pediatric patients 4 to less than 16 years of age receiving levetiracetam in combination with other AEDs, for events with rates greater than placebo, were fatigue, aggression, nasal congestion, decreased appetite, and irritability.

Table 6 lists adverse reactions from the pooled pediatric controlled studies (4 to less than 16 years of age) that occurred in at least 2% of pediatric levetiracetam-treated patients and were numerically more common than in pediatric patients treated with placebo. In these studies, either levetiracetam or placebo was added to concurrent AED therapy.

Table 6: Adverse Reactions in Pooled Placebo-Controlled, Adjunctive Studies in Pediatric Patients 4 to 16 Years of Age with Partial-Onset Seizures
Adverse Reaction | Levetiracetam (N=165) % | Placebo (N=131) %
Headache | 19 | 15
Nasopharyngitis | 15 | 12
Vomiting | 15 | 12
Somnolence | 13 | 9
Fatigue | 11 | 5
Aggression | 10 | 5
Cough | 9 | 5
Nasal Congestion | 9 | 2
Upper Abdominal Pain | 9 | 8
Decreased Appetite | 8 | 2
Abnormal Behavior | 7 | 4
Dizziness | 7 | 5
Irritability | 7 | 1
Pharyngolaryngeal Pain | 7 | 4
Diarrhea | 6 | 2
Lethargy | 6 | 5
Insomnia | 5 | 3
Agitation | 4 | 1
Anorexia | 4 | 3
Head Injury | 4 | 0
Altered Mood | 3 | 1
Constipation | 3 | 1
Contusion | 3 | 1
Depression | 3 | 1
Fall | 3 | 2
Influenza | 3 | 1
Affect Lability | 2 | 1
Anxiety | 2 | 1
Arthralgia | 2 | 0
Confusional State | 2 | 0
Conjunctivitis | 2 | 0
Ear Pain | 2 | 1
Gastroenteritis | 2 | 0
Joint Sprain | 2 | 1
Mood Swings | 2 | 1
Neck Pain | 2 | 1
Rhinitis | 2 | 0
Sedation | 2 | 1

In the controlled pooled pediatric clinical studies in patients 4 years to 16 years of age, 7% of patients receiving levetiracetam and 9% receiving placebo discontinued as a result of an adverse reaction.

Myoclonic Seizures

Although the pattern of adverse reactions in this study seems somewhat different from that seen in patients with partial-onset seizures, this is likely due to the much smaller number of patients in this study compared to partial seizure studies. The adverse reaction pattern for patients with JME is expected to be essentially the same as for patients with partial seizures.

In the controlled clinical study in patients 12 years of age and older with myoclonic seizures, [see Clinical Studies (14.2)], the most common adverse reactions in patients receiving levetiracetam in combination with other AEDs, for events with rates greater than placebo, were somnolence, neck pain, and pharyngitis.

Table 7 lists adverse reactions that occurred in at least 5% of juvenile myoclonic epilepsy patients experiencing myoclonic seizures treated with levetiracetam and were numerically more common than in patients treated with placebo. In this study, either levetiracetam or placebo was added to concurrent AED therapy.

Table 7: Adverse Reactions in a Placebo-Controlled, Adjunctive Study in Patients 12 Years of Age and Older with Myoclonic Seizures
Adverse Reaction | Levetiracetam (N=60) % | Placebo (N=60) %
Somnolence | 12 | 2
Neck pain | 8 | 2
Pharyngitis | 7 | 0
Depression | 5 | 2
Influenza | 5 | 2
Vertigo | 5 | 3

In the placebo-controlled study, 8% of patients receiving levetiracetam and 2% receiving placebo either discontinued or had a dose reduction as a result of an adverse reaction. The adverse reactions that led to discontinuation or dose reduction and that occurred more frequently in levetiracetam-treated patients than in placebo-treated patients are presented in Table 8.

Table 8: Adverse Reactions that Resulted in Discontinuation or Dose Reduction in a Placebo-Controlled Study in Patients with Juvenile Myoclonic Epilepsy
Adverse Reaction | Levetiracetam (N=60) % | Placebo (N=60) %
Anxiety | 3 | 2
Depressed mood | 2 | 0
Depression | 2 | 0
Diplopia | 2 | 0
Hypersomnia | 2 | 0
Insomnia | 2 | 0
Irritability | 2 | 0
Nervousness | 2 | 0
Somnolence | 2 | 0

Primary Generalized Tonic-Clonic Seizures

Although the pattern of adverse reactions in this study seems somewhat different from that seen in patients with partial-onset seizures, this is likely due to the much smaller number of patients in this study compared to partial seizure studies. The adverse reaction pattern for patients with primary generalized tonic-clonic (PGTC) seizures is expected to be essentially the same as for patients with partial seizures.

In the controlled clinical trial in patients with PGTC seizures [see Clinical Studies (14.3)], the most common adverse reaction in patients receiving levetiracetam in combination with other AEDs, for events with rates greater than placebo, was nasopharyngitis.

Table 9 lists adverse reactions that occurred in at least 5% of idiopathic generalized epilepsy patients experiencing PGTC seizures treated with levetiracetam and were numerically more common than in patients treated with placebo. In this study, either levetiracetam or placebo was added to concurrent AED therapy.

Table 9: Adverse Reactions in a Placebo-Controlled, Adjunctive Study in Patients 4 Years of Age and Older with PGTC Seizures
Adverse Reaction | Levetiracetam (N=79) % | Placebo (N=84) %
Nasopharyngitis | 14 | 5
Fatigue | 10 | 8
Diarrhea | 8 | 7
Irritability | 6 | 2
Mood swings | 5 | 1

In the placebo-controlled study, 5% of patients receiving levetiracetam and 8% receiving placebo either discontinued or had a dose reduction during the treatment period as a result of an adverse reaction.

This study was too small to adequately characterize the adverse reactions that could be expected to result in discontinuation of treatment in this population. It is expected that the adverse reactions that would lead to discontinuation in this population would be similar to those resulting in discontinuation in other epilepsy trials (see Table 5 and Table 8).

In addition, the following adverse reactions were seen in other controlled adult studies of levetiracetam: balance disorder, disturbance in attention, eczema, memory impairment, myalgia, and blurred vision.

Comparison of Gender, Age, and Race

The overall adverse reaction profile of levetiracetam was similar between females and males. There are insufficient data to support a statement regarding the distribution of adverse reactions by age and race.

6.2 Postmarketing Experience

The following adverse reactions have been identified during postapproval use of levetiracetam. Because these reactions are reported voluntarily from a population of uncertain size, it is not always possible to reliably estimate their frequency or establish a causal relationship to drug exposure.

The listing is alphabetized: abnormal liver function test, acute kidney injury, agranulocytosis, anaphylaxis, angioedema, choreoathetosis, drug reaction with eosinophilia and systemic symptoms (DRESS), dyskinesia, erythema multiforme, hepatic failure, hepatitis, hyponatremia, muscular weakness, obsessive-compulsive disorders (OCD), pancreatitis, pancytopenia (with bone marrow suppression identified in some of these cases), panic attack, thrombocytopenia, weight loss, and worsening of seizures including in patients with SCN8A mutations. Alopecia has been reported with levetiracetam use; recovery was observed in majority of cases where levetiracetam was discontinued.

8 USE IN SPECIFIC POPULATIONS

8.1 Pregnancy

Pregnancy Exposure Registry

There is a pregnancy exposure registry that monitors pregnancy outcomes in women exposed to antiepileptic drugs (AEDs), including SPRITAM, during pregnancy. Encourage women who are taking SPRITAM during pregnancy to enroll in the North American Antiepileptic Drug (NAAED) pregnancy registry by calling 1-888-233-2334 or visiting http://www.aedpregnancyregistry.org/.

Risk Summary

Prolonged experience with levetiracetam in pregnant women has not identified a drug-associated risk of major birth defects or miscarriage, based on published literature, which includes data from pregnancy registries and reflects experience over two decades [see Human Data]. In animal studies, levetiracetam produced developmental toxicity (increased embryofetal and offspring mortality, increased incidences of fetal structural abnormalities, decreased embryofetal and offspring growth, neurobehavioral alterations in offspring) at doses similar to human therapeutic doses [see Animal Data].

In the U.S. general population, the estimated background risk of major birth defects and miscarriage in clinically recognized pregnancies is 2-4% and 15-20%, respectively. The background risk of major birth defects and miscarriage for the indicated population is unknown.

Clinical Considerations

Levetiracetam blood levels may decrease during pregnancy [see Warnings and Precautions (5.11)].

Physiological changes during pregnancy may affect levetiracetam concentration. Decrease in levetiracetam plasma concentrations has been observed during pregnancy. This decrease is more pronounced during the third trimester. Dose adjustments may be necessary to maintain clinical response.

Data

Human Data

While available studies cannot definitively establish the absence of risk, data from the published literature and pregnancy registries have not established an association with levetiracetam use during pregnancy and major birth defects or miscarriage.

Animal Data

When levetiracetam (0, 400, 1200, or 3600 mg/kg/day) was administered orally to pregnant rats during the period of organogenesis, reduced fetal weights and increased incidence of fetal skeletal variations were observed at the highest dose tested. There was no evidence of maternal toxicity. The no-effect dose for adverse effects on embryofetal developmental in rats (1200/mg/kg/day) is approximately 4 times the maximum recommended human dose (MRHD) of 3000 mg on a body surface area (mg/m^2) basis.

Oral administration of levetiracetam (0, 200, 600, or 1800 mg/kg/day) to pregnant rabbits during the period of organogenesis resulted in increased embryofetal mortality and incidence of fetal skeletal variations at the mid and high dose and decreased fetal weights and increased incidence of fetal malformations at the high dose, which was associated with maternal toxicity. The no-effect dose for adverse effects on embryofetal development in rabbits (200 mg/kg/day) is approximately equivalent to the MRHD on a mg/m^2 basis.

Oral administration of levetiracetam (0, 70, 350, or 1800 mg/kg/day) to female rats throughout pregnancy and lactation led to an increased incidence of fetal skeletal variations, reduced fetal body weight, and decreased growth in offspring at the mid and high doses and increased pup mortality and neurobehavioral alterations in offspring at the highest dose tested. There was no evidence of maternal toxicity. The no-effect dose for adverse effects on pre- and postnatal development in rats (70 mg/kg/day) is less than the MRHD on a mg/m^2 basis.

Oral administration of levetiracetam to rats during the latter part of gestation and throughout lactation produced no adverse developmental or maternal effects at doses of up to 1800 mg/kg/day (6 times the MRHD on a mg/m^2 basis).

8.2 Lactation

Risk Summary

Levetiracetam is excreted in human milk. There are no data on the effects of levetiracetam on the breastfed infant, or the effects on milk production.

The developmental and health benefits of breastfeeding should be considered along with the mother’s clinical need for SPRITAM and any potential adverse effects on the breastfed infant from SPRITAM or from the underlying maternal condition.

8.4 Pediatric Use

SPRITAM is not recommended for pediatric patients that weigh 20 kg or less. The following sections describe age appropriate indications.

Partial-Onset Seizures

The safety and effectiveness of SPRITAM have been established for the treatment of partial-onset seizures in pediatric patients 4 years of age and older. Use is based on controlled studies in adult patients and efficacy data in 198 pediatric patients 4 to 16 years of age treated with levetiracetam with partial-onset seizures [see Clinical Pharmacology (12.3) and Clinical Studies (14.1)].

Safety and effectiveness for the treatment of partial-onset seizures in pediatric patients below the age of 4 years have not been established.

A 3-month, randomized, double-blind, placebo-controlled study was conducted to assess the neurocognitive and behavioral effects of levetiracetam as adjunctive therapy in 98 (levetiracetam N=64, placebo N=34) pediatric patients, 4 to 16 years of age, with partial seizures that were inadequately controlled. The target dose was 60 mg/kg/day. Neurocognitive effects were measured by the Leiter-R Attention and Memory (AM) Battery, which measures various aspects of a child's memory and attention. Although no substantive differences were observed between the placebo and drug treated groups in the median change from baseline in this battery, the study was not adequate to assess formal statistical non-inferiority of the drug and placebo. The Achenbach Child Behavior Checklist (CBCL/6-18), a standardized validated tool used to assess a child's competencies and behavioral/emotional problems, was also assessed in this study. An analysis of the CBCL/6-18 indicated on average a worsening in levetiracetam-treated patients in aggressive behavior, one of the eight syndrome scores [see Warnings and Precautions (5.1)].

Myoclonic Seizures

The safety and effectiveness of SPRITAM have been established as adjunctive treatment of myoclonic seizures in pediatric patients 12 years of age and older with juvenile myoclonic epilepsy. Use is based on one controlled study that included 113 adult and pediatric patients as young as 12 years of age treated with levetiracetam with juvenile myoclonic epilepsy [see Clinical Studies (14.2)].

Safety and effectiveness as adjunctive therapy for the treatment of myoclonic seizures in pediatric patients below the age of 12 years have not been established.

Primary Generalized Tonic-Clonic Seizures

The safety and effectiveness of SPRITAM have been established as adjunctive therapy in the treatment of primary generalized tonic-clonic seizures in pediatric patients 6 years of age and older with idiopathic generalized epilepsy. Use is based on one controlled study that included 164 adult and pediatric patients treated with levetiracetam with generalized tonic-clonic seizures [see Clinical Studies (14.3)].

Safety and effectiveness as adjunctive therapy for the treatment of primary generalized tonic-clonic seizures in pediatric patients below the age of 6 years have not been established.

Juvenile Animal Toxicity Data

Studies of levetiracetam in juvenile rats (dosed on postnatal days 4 through 52) and dogs (dosed from postnatal weeks 3 through 7) at doses of up to 1800 mg/kg/day (approximately 7 and 24 times, respectively, the maximum recommended pediatric dose of 60 mg/kg/day on a mg/m^2 basis) did not demonstrate adverse effects on postnatal development.

8.5 Geriatric Use

There were 347 subjects in clinical studies of levetiracetam that were 65 and over. No overall differences in safety were observed between these subjects and younger subjects. There were insufficient numbers of elderly subjects in controlled trials of epilepsy to adequately assess the effectiveness of levetiracetam in these patients.

Levetiracetam is known to be substantially excreted by the kidney, and the risk of adverse reactions to this drug may be greater in patients with renal impairment. Because elderly patients are more likely to have decreased renal function, care should be taken in dose selection, and it may be useful to monitor renal function [see Clinical Pharmacology (12.3)].

8.6 Renal Impairment

Clearance of levetiracetam is decreased in patients with renal impairment and is correlated with creatinine clearance [see Clinical Pharmacology (12.3)]. Dose adjustment is recommended for patients with renal impairment and supplemental doses should be given to patients after dialysis [see Dosage and Administration (2.3)].

10 OVERDOSAGE

10.1 Signs, Symptoms and Laboratory Findings of Acute Overdosage in Humans

The highest known dose of levetiracetam received in the clinical development program was 6000 mg/day. Other than drowsiness, there were no adverse reactions in the few known cases of overdose in clinical trials. Cases of somnolence, agitation, aggression, depressed level of consciousness, respiratory depression and coma were observed with levetiracetam overdoses in postmarketing use.

10.2 Management of Overdose

There is no specific antidote for overdose with SPRITAM. If indicated, elimination of unabsorbed drug should be attempted by emesis or gastric lavage; usual precautions should be observed to maintain airway. General supportive care of the patient is indicated including monitoring of vital signs and observation of the patient's clinical status. A Certified Poison Control Center should be contacted for up to date information on the management of overdose with SPRITAM.

10.3 Hemodialysis

Standard hemodialysis procedures result in significant clearance of levetiracetam (approximately 50% in 4 hours) and should be considered in cases of overdose. Although hemodialysis has not been performed in the few known cases of overdose, it may be indicated by the patient's clinical state or in patients with significant renal impairment.

11 DESCRIPTION

SPRITAM (levetiracetam) is an antiepileptic drug available as 250 mg and 500 mg round, white to off-white, spearmint-flavored tablets for oral suspension.

The chemical name of levetiracetam, a single enantiomer, is (-)-(S)-α-ethyl-2-oxo-1-pyrrolidine acetamide, its molecular formula is C8H14N2O2 and its molecular weight is 170.21. It has the following structural formula:

Levetiracetam is a white to off-white crystalline powder with a faint odor and a bitter taste. It is very soluble in water (104.0 g/100 mL). It is freely soluble in chloroform (65.3 g/100 mL) and in methanol (53.6 g/100 mL), soluble in ethanol (16.5 g/100 mL), sparingly soluble in acetonitrile (5.7 g/100 mL) and practically insoluble in n-hexane. (Solubility limits are expressed as g/100 mL solvent).

SPRITAM tablets for oral suspension contain 250 mg and 500 mg levetiracetam. Each tablet also contains the following inactive ingredients: colloidal silicon dioxide, glycerin, mannitol, microcrystalline cellulose, polysorbate 20, povidone, sucralose, butylated hydroxyanisole, and natural and artificial spearmint flavor.

SPRITAM tablets for oral suspension are unitary porous structures produced by a three-dimensional printing process that binds the powders without compression.

SPRITAM tablets for oral suspension disintegrate in a mean time of 11 seconds (ranging from 2 to 27 seconds) in the mouth, when taken with a sip of liquid, to produce small particles that may be swallowed.

12 CLINICAL PHARMACOLOGY

12.1 Mechanism of Action

The precise mechanism(s) by which levetiracetam exerts its antiepileptic effect is unknown.

A saturable and stereoselective neuronal binding site in rat brain tissue has been described for levetiracetam. Experimental data indicate that this binding site is the synaptic vesicle protein SV2A, thought to be involved in the regulation of vesicle exocytosis. Although the molecular significance of levetiracetam binding to SV2A is not understood, levetiracetam and related analogs showed a rank order of affinity for SV2A which correlated with the potency of their antiseizure activity in audiogenic seizure-prone mice. These findings suggest that the interaction of levetiracetam with the SV2A protein may contribute to the antiepileptic mechanism of action of the drug.

12.2 Pharmacodynamics

Effects on QTc Interval

The effect of levetiracetam on QTc prolongation was evaluated in a randomized, double-blind, positive-controlled (moxifloxacin 400 mg) and placebo-controlled crossover study of levetiracetam (1000 mg or 5000 mg) in 52 healthy subjects. The upper bound of the 90% confidence interval for the largest placebo-adjusted, baseline-corrected QTc was below 10 milliseconds. Therefore, there was no evidence of significant QTc prolongation in this study.

12.3 Pharmacokinetics

The pharmacokinetics of levetiracetam are similar when used as monotherapy or as adjunctive therapy for the treatment of partial-onset seizures.

Absorption and Distribution

Peak plasma concentrations of levetiracetam occurred in about an hour following oral administration in fasted subjects. In a crossover study in healthy volunteers, SPRITAM, administered with a sip of water, was shown to have equivalent rate and extent of absorption to levetiracetam immediate release tablets, administered with a glass of water under fasting conditions. High fat meal does not affect the extent of absorption of SPRITAM but it decreases Cmax by 36% and delays tmax by 3.4 hours.

The oral bioavailability of levetiracetam tablets is 100% and the tablets and oral solution are bioequivalent in rate and extent of absorption. Food does not affect the extent of absorption of levetiracetam but it decreases Cmax by 20% and delays tmax by 1.5 hours. The pharmacokinetics of levetiracetam are linear over the dose range of 500-5000 mg. Steady state is achieved after 2 days of multiple twice-daily dosing. Levetiracetam and its major metabolite are less than 10% bound to plasma proteins; clinically significant interactions with other drugs through competition for protein binding sites are therefore unlikely.

Metabolism

Levetiracetam is not extensively metabolized in humans. The major metabolic pathway is the enzymatic hydrolysis of the acetamide group, which produces the carboxylic acid metabolite, ucb L057 (24% of dose) and is not dependent on any liver cytochrome P450 isoenzymes. The major metabolite is inactive in animal seizure models. Two minor metabolites were identified as the product of hydroxylation of the 2-oxo-pyrrolidine ring (2% of dose) and opening of the 2‑oxo‑pyrrolidine ring in position 5 (1% of dose). There is no enantiomeric interconversion of levetiracetam or its major metabolite.

Elimination

Levetiracetam plasma half-life in adults is 7 ± 1 hour and is unaffected by either dose or repeated administration. Levetiracetam is eliminated from the systemic circulation by renal excretion as unchanged drug which represents 66% of administered dose. The total body clearance is 0.96 mL/min/kg and the renal clearance is 0.6 mL/min/kg. The mechanism of excretion is glomerular filtration with subsequent partial tubular reabsorption. The metabolite ucb L057 is excreted by glomerular filtration and active tubular secretion with a renal clearance of 4 mL/min/kg. Levetiracetam elimination is correlated to creatinine clearance. Levetiracetam clearance is reduced in patients with renal impairment [see Dosage and Administration (2.3), Use in Specific Populations (8.6)].

Specific Populations

Elderly

Pharmacokinetics of levetiracetam were evaluated in 16 elderly subjects (61-88 years of age) with creatinine clearance ranging from 30 to 74 mL/min. Following oral administration of twice‑daily dosing for 10 days, total body clearance decreased by 38% and the half-life was 2.5 hours longer in the elderly compared to healthy adults. This is most likely due to the decrease in renal function in these subjects.

Pediatric Patients

Pharmacokinetics of levetiracetam were evaluated in 24 pediatric patients (6-12 years of age) after single dose (20 mg/kg). The body weight adjusted apparent clearance of levetiracetam was approximately 40% higher than in adults.

A repeat dose pharmacokinetic study was conducted in pediatric patients (4-12 years of age) at doses of 20 mg/kg/day, 40 mg/kg/day, and 60 mg/kg/day. The evaluation of the pharmacokinetic profile of levetiracetam and its metabolite (ucb L057) in 14 pediatric patients demonstrated rapid absorption of levetiracetam at all doses with a tmax of about 1 hour and a t½ of 5 hours across the three dosing levels. The pharmacokinetics of levetiracetam in pediatric patients was linear between 20 to 60 mg/kg/day. The potential interaction of levetiracetam with other AEDs was also evaluated in these patients. Levetiracetam had no significant effect on the plasma concentrations of carbamazepine, valproic acid, topiramate, or lamotrigine. However, there was about a 22% increase of apparent clearance of levetiracetam when it was co‑administered with an enzyme-inducing AED (e.g., carbamazepine).

Population pharmacokinetic analysis showed that body weight was significantly correlated to the clearance of levetiracetam in pediatric patients; clearance increased with an increase in body weight.

Pediatric Patients with Obesity

A population PK analysis of levetiracetam was conducted in 164 obese and non-obese pediatric patients 2 to <18 years of age with median (range) weight 39.2 (11.3-134) kg to evaluate the potential impact of obesity on plasma levetiracetam exposures. Obesity was defined as BMI ≥95th percentile for age and sex based on CDC 2000 growth chart recommendations. Simulations were conducted for obese and non-obese pediatric patients ages 4 to <16 years.

- When the recommended tablet dose is administered to pediatric patients weighing < 40 kg, obese pediatric patients have 27% higher median Cmax,ss, and 19% higher median Cmin,ss compared to non-obese patients.
- When the recommended tablet dose is administered to pediatric patients weighing ≥ 40 kg, obese pediatric patients have 10-11% lower median Cmax,ss and 2% lower median Cmin,ss compared to non-obese patients.
- When the recommended oral solution dose is administered to pediatric patients across the full weight range, obese pediatric patients have 25% higher median Cmax,ss and 41% higher median Cmin,ss compared to non-obese pediatric patients.

However, differences in exposures between obese and non-obese pediatric patients are not expected to be clinically meaningful because the recommended dose titration at initiation of levetiracetam therapy would establish an appropriate dose for each individual patient.

Pregnancy

Levetiracetam levels may decrease during pregnancy [see Warnings and Precautions (5.11) and Use in Specific Populations (8.1)].

Gender

Levetiracetam Cmax and AUC were 20% higher in women (N=11) compared to men (N=12). However, clearances adjusted for body weight were comparable.

Race

Formal pharmacokinetic studies of the effects of race have not been conducted. Cross study comparisons involving Caucasians (N=12) and Asians (N=12), however, show that pharmacokinetics of levetiracetam were comparable between the two races. Because levetiracetam is primarily renally excreted and there are no important racial differences in creatinine clearance, pharmacokinetic differences due to race are not expected.

Renal Impairment

The disposition of levetiracetam was studied in adult subjects with varying degrees of renal function. Total body clearance of levetiracetam is reduced in patients with impaired renal function by 40% in the mild group (CLcr = 50-80 mL/min), 50% in the moderate group (CLcr = 30-50 mL/min), and 60% in the severe renal impairment group (CLcr < 30 mL/min). Clearance of levetiracetam is correlated with creatinine clearance.

In anuric (end stage renal disease) patients, the total body clearance decreased 70% compared to normal subjects (CLcr > 80 mL/min). Approximately 50% of the pool of levetiracetam in the body is removed during a standard 4-hour hemodialysis procedure [see Dosage and Administration (2.3)].

Hepatic Impairment

In subjects with mild (Child-Pugh A) to moderate (Child-Pugh B) hepatic impairment, the pharmacokinetics of levetiracetam were unchanged. In patients with severe hepatic impairment (Child-Pugh C), total body clearance was 50% that of normal subjects, but decreased renal clearance accounted for most of the decrease. No dose adjustment is needed for patients with hepatic impairment.

Drug Interactions

In vitro data on metabolic interactions indicate that levetiracetam is unlikely to produce, or be subject to, pharmacokinetic interactions. Levetiracetam and its major metabolite, at concentrations well above Cmax levels achieved within the therapeutic dose range, are neither inhibitors of, nor high affinity substrates for, human liver cytochrome P450 isoforms, epoxide hydrolase or UDP-glucuronidation enzymes. In addition, levetiracetam does not affect the in vitro glucuronidation of valproic acid.

Potential pharmacokinetic interactions of or with levetiracetam were assessed in clinical pharmacokinetic studies (phenytoin, valproate, warfarin, digoxin, oral contraceptive, probenecid) and through pharmacokinetic screening in the placebo-controlled clinical studies in epilepsy patients.

Phenytoin

Levetiracetam (3000 mg daily) had no effect on the pharmacokinetic disposition of phenytoin in patients with refractory epilepsy. Pharmacokinetics of levetiracetam were also not affected by phenytoin.

Valproate

Levetiracetam (1500 mg twice daily) did not alter the pharmacokinetics of valproate in healthy volunteers. Valproate 500 mg twice daily did not modify the rate or extent of levetiracetam absorption or its plasma clearance or urinary excretion. There also was no effect on exposure to and the excretion of the primary metabolite, ucb L057.

Other Antiepileptic Drugs

Potential drug interactions between levetiracetam and other AEDs (carbamazepine, gabapentin, lamotrigine, phenobarbital, phenytoin, primidone, and valproate) were also assessed by evaluating the serum concentrations of levetiracetam and these AEDs during placebo-controlled clinical studies. These data indicate that levetiracetam does not influence the plasma concentration of other AEDs and that these AEDs do not influence the pharmacokinetics of levetiracetam.

Effect of AEDs in Pediatric Patients

There was about a 22% increase of apparent total body clearance of levetiracetam when it was co-administered with enzyme-inducing AEDs. Dose adjustment is not recommended. Levetiracetam had no effect on plasma concentrations of carbamazepine, valproate, topiramate, or lamotrigine.

Oral Contraceptives

Levetiracetam (500 mg twice daily) did not influence the pharmacokinetics of an oral contraceptive containing 0.03 mg ethinyl estradiol and 0.15 mg levonorgestrel, or of the luteinizing hormone and progesterone levels, indicating that impairment of contraceptive efficacy is unlikely. Coadministration of this oral contraceptive did not influence the pharmacokinetics of levetiracetam.

Digoxin

Levetiracetam (1000 mg twice daily) did not influence the pharmacokinetics and pharmacodynamics (ECG) of digoxin given as a 0.25 mg dose every day. Coadministration of digoxin did not influence the pharmacokinetics of levetiracetam.

Warfarin

Levetiracetam (1000 mg twice daily) did not influence the pharmacokinetics of R and S warfarin. Prothrombin time was not affected by levetiracetam. Coadministration of warfarin did not affect the pharmacokinetics of levetiracetam.

Probenecid

Probenecid, a renal tubular secretion blocking agent, administered at a dose of 500 mg four times a day, did not change the pharmacokinetics of levetiracetam 1000 mg twice daily. Cssmax of the metabolite, ucb L057, was approximately doubled in the presence of probenecid while the fraction of drug excreted unchanged in the urine remained the same. Renal clearance of ucb L057 in the presence of probenecid decreased 60%, probably related to competitive inhibition of tubular secretion of ucb L057. The effect of levetiracetam on probenecid was not studied.

13 NONCLINICAL TOXICOLOGY

13.1 Carcinogenesis, Mutagenesis, Impairment of Fertility

Carcinogenesis

Rats were dosed with levetiracetam in the diet for 104 weeks at doses of 50, 300 and 1800 mg/kg/day. Plasma exposure (AUC) at the highest dose was approximately 6 times that in humans at the maximum recommended daily human dose (MRHD) of 3000 mg. There was no evidence of carcinogenicity. In mice, oral administration of levetiracetam for 80 weeks (doses up to 960 mg/kg/day) or 2 years (doses up to 4000 mg/kg/day, lowered to 3000 mg/kg/day after 45 weeks due to intolerability) was not associated with an increase in tumors. The highest dose tested in mice for 2 years (3000 mg/kg/day) is approximately 5 times the MRHD on a body surface area (mg/m^2) basis.

Mutagenesis

Levetiracetam was negative in in vitro (Ames, chromosomal aberration in mammalian cells) and in vivo (mouse micronucleus) assays. The major human metabolite of levetiracetam (ucb L057) was negative in in vitro (Ames, mouse lymphoma) assays.

Impairment of Fertility

No adverse effects on male or female fertility or reproductive performance were observed in rats at oral doses up to 1800 mg/kg/day, which were associated with plasma exposures (AUC) up to approximately 6 times that in humans at the MRHD.

14 CLINICAL STUDIES

The efficacy of SPRITAM is based upon bioavailability studies in healthy subjects comparing oral levetiracetam tablets to SPRITAM.

14.1 Partial-Onset Seizures

Effectiveness in Partial-Onset Seizures in Adults

The effectiveness of levetiracetam for the treatment of partial-onset seizures in adults was established in three multicenter, randomized, double-blind, placebo-controlled clinical studies in patients who had refractory partial-onset seizures with or without secondary generalization. The tablet formulation was used in all these studies. In these studies, 904 patients were randomized to placebo, 1000 mg, 2000 mg, or 3000 mg/day. Patients enrolled in Study 1 or Study 2 had refractory partial-onset seizures for at least two years and had taken two or more classical AEDs. Patients enrolled in Study 3 had refractory partial-onset seizures for at least 1 year and had taken one classical AED. At the time of the study, patients were taking a stable dose regimen of at least one and could take a maximum of two AEDs. During the baseline period, patients had to have experienced at least two partial-onset seizures during each 4-week period.

Study 1

Study 1 was a double-blind, placebo-controlled, parallel-group study conducted at 41 sites in the United States comparing levetiracetam 1000 mg/day (N=97), levetiracetam 3000 mg/day (N=101), and placebo (N=95) given in equally divided doses twice daily. After a prospective baseline period of 12 weeks, patients were randomized to one of the three treatment groups described above. The 18-week treatment period consisted of a 6-week titration period, followed by a 12-week fixed dose evaluation period, during which concomitant AED regimens were held constant. The primary measure of effectiveness was a between group comparison of the percent reduction in weekly partial seizure frequency relative to placebo over the entire randomized treatment period (titration + evaluation period). Secondary outcome variables included the responder rate (incidence of patients with ≥ 50% reduction from baseline in partial-onset seizure frequency). The results of the analysis of Study 1 are displayed in Table 10.

Table 10: Reduction In Mean Over Placebo In Weekly Frequency Of Partial-Onset Seizures In Study 1
 | Placebo (N=95) | Levetiracetam 1000 mg/day (N=97) | Levetiracetam 3000 mg/day (N=101)
Percent reduction in partial seizure frequency over placebo | _ | 26%^1 | 30%^1
^1 Statistically significant versus placebo

The percentage of patients (y-axis) who achieved ≥ 50% reduction in weekly seizure rates from baseline in partial-onset seizure frequency over the entire randomized treatment period (titration + evaluation period) within the three treatment groups (x-axis) is presented in Figure 1.

Figure 1: Responder Rate (≥ 50% Reduction From Baseline) In Study 1

*Statistically significant versus placebo

Study 2

Study 2 was a double-blind, placebo-controlled, crossover study conducted at 62 centers in Europe comparing levetiracetam 1000 mg/day (N=106), levetiracetam 2000 mg/day (N=105), and placebo (N=111) given in equally divided doses twice daily.

The first period of the study (Period A) was designed to be analyzed as a parallel-group study. After a prospective baseline period of up to 12 weeks, patients were randomized to one of the three treatment groups described above. The 16-week treatment period consisted of the 4-week titration period followed by a 12-week fixed dose evaluation period, during which concomitant AED regimens were held constant. The primary measure of effectiveness was a between group comparison of the percent reduction in weekly partial seizure frequency relative to placebo over the entire randomized treatment period (titration + evaluation period). Secondary outcome variables included the responder rate (incidence of patients with ≥ 50% reduction from baseline in partial-onset seizure frequency). The results of the analysis of Period A are displayed in Table 11.

Table 11: Reduction In Mean Over Placebo In Weekly Frequency Of Partial-Onset Seizures In Study 2: Period A
 | Placebo (N=111) | Levetiracetam 1000 mg/day (N=106) | Levetiracetam 2000 mg/day (N=105)
Percent reduction in partial seizure frequency over placebo | _ | 17%^1 | 21%^1
^1 Statistically significant versus placebo

The percentage of patients (y-axis) who achieved ≥ 50% reduction in weekly seizure rates from baseline in partial-onset seizure frequency over the entire randomized treatment period (titration + evaluation period) within the three treatment groups (x-axis) is presented in Figure 2.

Figure 2: Responder Rate (≥ 50% Reduction From Baseline) In Study 2: Period A

*Statistically significant versus placebo

The comparison of levetiracetam 2000 mg/day to levetiracetam 1000 mg/day for responder rate was statistically significant (P=0.02). Analysis of the trial as a cross-over yielded similar results.

Study 3

Study 3 was a double-blind, placebo-controlled, parallel-group study conducted at 47 centers in Europe comparing levetiracetam 3000 mg/day (N=180) and placebo (N=104) in patients with refractory partial-onset seizures, with or without secondary generalization, receiving only one concomitant AED. Study drug was given in two divided doses. After a prospective baseline period of 12 weeks, patients were randomized to one of two treatment groups described above. The 16-week treatment period consisted of a 4-week titration period, followed by a 12-week fixed dose evaluation period, during which concomitant AED doses were held constant. The primary measure of effectiveness was a between group comparison of the percent reduction in weekly seizure frequency relative to placebo over the entire randomized treatment period (titration + evaluation period). Secondary outcome variables included the responder rate (incidence of patients with ≥ 50% reduction from baseline in partial-onset seizure frequency). Table 12 displays the results of the analysis of Study 3.

Table 12: Reduction In Mean Over Placebo In Weekly Frequency Of Partial-Onset Seizures In Study 3
 | Placebo (N=104) | Levetiracetam 3000 mg/day (N=180)
Percent reduction in partial seizure frequency over placebo | _ | 23%^1
^1 Statistically significant versus placebo

The percentage of patients (y-axis) who achieved ≥ 50% reduction in weekly seizure rates from baseline in partial-onset seizure frequency over the entire randomized treatment period (titration + evaluation period) within the two treatment groups (x-axis) is presented in Figure 3.

Figure 3: Responder Rate (≥ 50% Reduction From Baseline) In Study 3

*Statistically significant versus placebo

Effectiveness in Partial-Onset Seizures in Pediatric Patients 4 to 16 Years of Age

The effectiveness of levetiracetam for the treatment of partial-onset seizures in pediatric patients was established in one multicenter, randomized double-blind, placebo controlled study (Study 4), conducted at 60 sites in North America, in pediatric patients 4 to 16 years of age with partial seizures uncontrolled by standard antiepileptic drugs (AEDs). Eligible patients on a stable dose of 1-2 AEDs, who still experienced at least 4 partial-onset seizures during the 4 weeks prior to screening, as well as at least 4 partial-onset seizures in each of the two 4-week baseline periods, were randomized to receive either levetiracetam or placebo. The enrolled population included 198 patients (levetiracetam N=101, placebo N=97) with refractory partial-onset seizures, whether or not secondarily generalized. The study consisted of an 8-week baseline period and 4-week titration period followed by a 10-week evaluation period. Dosing was initiated at a dose of 20 mg/kg/day in two divided doses. During the treatment period, levetiracetam doses were adjusted in 20 mg/kg/day increments, at 2-week intervals to the target dose of 60 mg/kg/day. The primary measure of effectiveness was a between group comparison of the percent reduction in weekly partial seizure frequency relative to placebo over the entire 14 week randomized treatment period (titration + evaluation period). Secondary outcome variables included the responder rate (incidence of patients with ≥ 50% reduction from baseline in partial-onset seizure frequency per week). Table 13 displays the results of this study.

Table 13: Reduction In Mean Over Placebo In Weekly Frequency Of Partial-Onset Seizures in Study 4
 | Placebo (N=97) | Levetiracetam (N=101)
Percent reduction in partial seizure frequency over placebo | _ | 27%^1
^1 Statistically significant versus placebo

The percentage of patients (y-axis) who achieved ≥ 50% reduction in weekly seizure rates from baseline in partial-onset seizure frequency over the entire randomized treatment period (titration + evaluation period) within the two treatment groups (x-axis) is presented in Figure 4.

Figure 4: Responder Rate (≥ 50% Reduction From Baseline) in Study 4

*Statistically significant versus placebo

14.2 Myoclonic Seizures in Patients with Juvenile Myoclonic Epilepsy

The effectiveness of levetiracetam as adjunctive therapy in patients 12 years of age and older with juvenile myoclonic epilepsy (JME) experiencing myoclonic seizures was established in one multicenter, randomized, double-blind, placebo controlled study (Study 6), conducted at 37 sites in 14 countries. Eligible patients on a stable dose of 1 antiepileptic drug (AED) experiencing one or more myoclonic seizures per day for at least 8 days during the prospective 8-week baseline period were randomized to either levetiracetam or placebo (levetiracetam N=60, placebo N=60). Patients were titrated over 4 weeks to a target dose of 3000 mg/day and treated at a stable dose of 3000 mg/day over 12 weeks (evaluation period). Study drug was given in 2 divided doses.

The primary measure of effectiveness was the proportion of patients with at least 50% reduction in the number of days per week with one or more myoclonic seizures during the treatment period (titration + evaluation periods) as compared to baseline. Of the 120 patients enrolled, 113 had a diagnosis of confirmed or suspected JME. Table 14 displays the results for the 113 patients with JME in this study.

Table 14: Responder Rate (≥ 50% Reduction From Baseline) In Myoclonic Seizure Days Per Week for Patients with JME in Study 6
 | Placebo (N=59) | Levetiracetam (N=54)
Percentage of responders | 24% | 60%^1
^1 Statistically significant versus placebo

14.3 Primary Generalized Tonic-Clonic Seizures

The effectiveness of levetiracetam as adjunctive therapy in patients 6 years of age and older with idiopathic generalized epilepsy experiencing primary generalized tonic-clonic (PGTC) seizures was established in one multicenter, randomized, double-blind, placebo-controlled study (Study 7), conducted at 50 sites in 8 countries. Eligible patients, 6 years of age and older, on a stable dose of 1 or 2 antiepileptic drugs (AEDs) experiencing at least 3 PGTC seizures during the 8-week combined baseline period (at least one PGTC seizure during the 4 weeks prior to the prospective baseline period and at least one PGTC seizure during the 4-week prospective baseline period) were randomized to either levetiracetam or placebo. The 8-week combined baseline period is referred to as "baseline" in the remainder of this section. The population included 164 patients (levetiracetam N=80, placebo N=84) with idiopathic generalized epilepsy (predominately juvenile myoclonic epilepsy, juvenile absence epilepsy, childhood absence epilepsy, or epilepsy with Grand Mal seizures on awakening) experiencing primary generalized tonic-clonic seizures. Each of these syndromes of idiopathic generalized epilepsy was well represented in this patient population. Patients were titrated over 4 weeks to a target dose of 3000 mg/day for adults or a pediatric target dose of 60 mg/kg/day and treated at a stable dose of 3000 mg/day (or 60 mg/kg/day for children) over 20 weeks (evaluation period). Study drug was given in 2 equally divided doses per day. The primary measure of effectiveness was the percent reduction from baseline in weekly PGTC seizure frequency for levetiracetam and placebo treatment groups over the treatment period (titration + evaluation periods).

There was a statistically significant decrease from baseline in PGTC frequency in the levetiracetam-treated patients compared to the placebo-treated patients as summarized below in Table 15.

Table 15: Median Percent Reduction From Baseline In PGTC Seizure Frequency Per Week in Study 7
 | Placebo (N=84) | Levetiracetam (N=78)
Percent reduction in PGTC seizure frequency | 45% | 78%^1
^1 Statistically significant versus placebo

The percentage of patients (y-axis) who achieved ≥ 50% reduction in weekly seizure rates from baseline in PGTC seizure frequency over the entire randomized treatment period (titration + evaluation period) within the two treatment groups (x-axis) is presented in Figure 5.

Figure 5: Responder Rate (≥ 50% Reduction From Baseline) In PGTC Seizure Frequency Per Week in Study 7

*Statistically significant versus placebo

16 HOW SUPPLIED/STORAGE AND HANDLING

16.1 How Supplied

SPRITAM (levetiracetam) tablet(s) for oral suspension are supplied in child-resistant blisters as follows:

250 mg: round, white to off‑white, spearmint‑flavored tablets, marked with "" on one side

- Commercial Use: 60 tablets per carton (6 tablets per blister card x 10 cards)
  (NDC 43485-101-60)
- Institutional Use: 6 tablets per carton (6 tablets per blister card x 1 card)
  (NDC 43485-101-03)

500 mg: round, white to off‑white, spearmint‑flavored tablets, marked with "" on one side

- Commercial Use: 60 tablets per carton (6 tablets per blister card x 10 cards)
  (NDC 43485-102-60)
- Institutional Use: 6 tablets per carton (6 tablets per blister card x 1 card)
  (NDC 43485-102-03)

16.2 Storage

Store at 25°C (77°F); excursions permitted to 15°C to 30°C (59°F to 86°F) [see USP Controlled Room Temperature].

17 PATIENT COUNSELING INFORMATION

Advise the patient to read the FDA-approved patient labeling (Medication Guide).

Psychiatric Reactions and Changes in Behavior

Advise patients that SPRITAM may cause changes in behavior (e.g. aggression, agitation, anger, anxiety, apathy, depression, hostility, and irritability) and psychotic symptoms [see Warnings and Precautions (5.1)].

Suicidal Behavior and Ideation

Counsel patients, their caregivers, and/or families that antiepileptic drugs (AEDs), including SPRITAM, may increase the risk of suicidal thoughts and behavior and advise patients to be alert for the emergence or worsening of symptoms of depression; unusual changes in mood or behavior; or suicidal thoughts, behavior, or thoughts about self-harm. Advise patients, their caregivers, and/or families to immediately report behaviors of concern to a healthcare provider [see Warnings and Precautions (5.2)].

Effects on Driving or Operating Machinery

Inform patients that SPRITAM may cause dizziness and somnolence. Inform patients not to drive or operate machinery until they have gained sufficient experience on SPRITAM to gauge whether it adversely affects their ability to drive or operate machinery [see Warnings and Precautions (5.3)]

Anaphylaxis and Angioedema

Advise patients to discontinue SPRITAM and seek medical care if they develop signs and symptoms of anaphylaxis or angioedema [see Warnings and Precautions (5.4)]

Dermatological Adverse Reactions

Advise patients that serious dermatological adverse reactions have occurred in patients treated with SPRITAM and instruct them to call their physician immediately if a rash develops [see Warnings and Precautions (5.5)]

DRESS/Multiorgan Hypersensitivity

Instruct patients and caregivers that a fever or rash associated with signs of other organ system involvement (e.g., lymphadenopathy, hepatic dysfunction) may be drug-related and should be reported to their healthcare provider immediately. SPRITAM should be discontinued immediately if a serious hypersensitivity reaction is suspected [see Warnings and Precautions (5.6)].

Withdrawal of SPRITAM

Advise patients and caregivers not to discontinue use of SPRITAM without consulting with their healthcare provider. SPRITAM should normally be gradually withdrawn to reduce the potential of increased seizure frequency and status epilepticus [see Warnings and Precautions (5.8)].

Pregnancy

Advise patients to notify their healthcare provider if they become pregnant or intend to become pregnant during SPRITAM therapy. Encourage patients to enroll in the North American Antiepileptic Drug (NAAED) pregnancy registry if they become pregnant. [see Use in Specific Populations (8.1)].

Preparation and Administration Information

Instruct patients to administer SPRITAM with or without food, and not to administer partial tablets [see Dosage and Administration (2.1)]. Instruct patients to peel the foil from the blister by bending up and lifting the peel tab around the blister seal.
Instruct patients on the appropriate method of administration:

1. Place tablet on the tongue with a dry hand, follow with a sip of liquid and swallow only after the tablet disintegrates. Advise patients not to swallow SPRITAM intact; or

2. Alternately, add whole SPRITAM tablet(s) to a small volume of liquid in a cup (one tablespoon or enough to cover the medicine). Advise patients to allow the tablet(s) to fully disperse, and then immediately consume the entire contents by mouth using the cup or oral syringe. After administration of the suspension, re-suspend any residue by adding an additional small volume of liquid, and swallow the full amount; or

3. SPRITAM can be administered using a nasogastric tube (NG tube) or gastrostomy tube (G tube) [see Dosage and Administration (2.1)].

Manufactured by Aprecia Pharmaceuticals, LLC, Mason, OH 45040 USA

Distributed by Prasco, LLC, Mason, OH 45040 USA

SPRITAM® is a registered trademark of Aprecia Pharmaceuticals, LLC.

© 2025 Aprecia Pharmaceuticals, LLC all rights reserved.

Printed in the USA

Patent(s): www.aprecia.com/patents

LB-PI-0001.U

MEDICATION GUIDE
SPRITAM® (SPREE-tam)
(levetiracetam)
tablets, for oral suspension

What is the most important information I should know about SPRITAM?
Like other antiepileptic drugs, SPRITAM may cause suicidal thoughts or actions in a very small number of people, about 1 in 500 people taking it.
Call a healthcare provider right away if you have any of these symptoms, especially if they are new, worse, or worry you:

- thoughts about suicide or dying
- new or worse depression
- feeling agitated or restless
- trouble sleeping (insomnia)
- acting aggressive, being angry, or violent
- an extreme increase in activity or talking (mania)
- attempts to commit suicide
- new or worse anxiety
- panic attacks
- new or worse irritability
- acting on dangerous impulses
- other unusual changes in behavior or mood

Do not stop SPRITAM without first talking to a healthcare provider.

- Stopping SPRITAM suddenly can cause serious problems. Stopping a seizure medicine suddenly can cause seizures that will not stop (status epilepticus).
- Suicidal thoughts or actions can be caused by things other than medicines. If you have suicidal thoughts or actions, your healthcare provider may check for other causes.

How can I watch for early symptoms of suicidal thoughts and actions?

- Pay attention to any changes, especially sudden changes, in mood, behaviors, thoughts, or feelings.
- Keep all follow-up visits with your healthcare provider as scheduled.
- Call your healthcare provider between visits as needed, especially if you are worried about symptoms.

What is SPRITAM?

SPRITAM is a prescription medicine taken by mouth that is used to treat partial-onset seizures in people 4 years of age and older weighing more than 44 pounds (20 kilograms).
SPRITAM is a prescription medicine taken by mouth that is used with other medicines to treat:

- myoclonic seizures in people 12 years of age and older with juvenile myoclonic epilepsy.
- primary generalized tonic-clonic seizures in people 6 years of age and older with certain types of generalized epilepsy.

It is not known if SPRITAM is safe or effective in children under:

- 4 years of age to treat partial-onset seizures
- 12 years of age to treat myoclonic seizures
- 6 years of age to treat primary generalized tonic-clonic seizures

SPRITAM is not recommended for children that weigh 44 pounds (20 kilograms) or less.

Before taking your medicine, make sure you have received the correct medicine. Compare the name above with the name on your carton (box). Tell your pharmacist immediately if you think you have been given the wrong medicine.

Who should not take SPRITAM?

Do not take SPRITAM if you are allergic to levetiracetam.

What should I tell my healthcare provider before starting SPRITAM?

Before taking SPRITAM, tell your healthcare provider about all of your medical conditions, including if you:

- have or have had depression, mood problems or suicidal thoughts or behavior.
- have kidney problems.
- are pregnant or planning to become pregnant. It is not known if SPRITAM will harm your unborn baby. You and your healthcare provider will have to decide if you should take SPRITAM while you are pregnant. If you become pregnant while taking SPRITAM, talk to your healthcare provider about registering with the North American Antiepileptic Drug Pregnancy Registry. You can enroll in this registry by calling 1-888-233-2334 or go to http://www.aedpregnancyregistry.org. The purpose of the registry is to collect information about the safety of SPRITAM and other antiepileptic medicine during pregnancy.
- are breastfeeding or plan to breastfeed. SPRITAM can pass into your breast milk. It is not known if the SPRITAM that passes into your breast milk can harm your baby. Talk to your doctor about the best way to feed your baby while you receive SPRITAM.

Tell your healthcare provider about all the medicines you take, including prescription and over-the-counter medicines, vitamins, and herbal supplements. Do not start a new medicine without first talking with your healthcare provider.

Know the medicines you take. Keep a list of them to show your healthcare provider and pharmacist each time you get a new medicine.

How should I take SPRITAM?

- Take SPRITAM exactly as your healthcare provider tells you to take it.
- Your healthcare provider will tell you how much SPRITAM to take and when to take it. SPRITAM is usually taken 2 times each day.
- Your healthcare provider may change your dose. Do not change your dose without talking to your healthcare provider.
- The main way to take SPRITAM is by letting the tablet dissolve (disintegrate) in your mouth with a sip of liquid.
- Another way to take SPRITAM is by adding the whole tablet or tablets to a small amount of liquid in a cup.
- You may also give SPRITAM using a Nasogastric Tube (NG Tube) or Gastrostomy Tube (G-Tube).
- Make sure your hands are dry before you remove your SPRITAM tablet or tablets.
- Do not push the tablet through the foil packaging.
- Peel the foil away from the blister by bending up and lifting the peel tab around the blister seal.
- Take the whole tablet as instructed below. Do not break up the tablet.
  - How to take SPRITAM with a sip of liquid:
    - Empty the tablet into your dry hand. Do not swallow the tablet whole.
    - Place the SPRITAM tablet on your tongue and follow with a sip of liquid. Before swallowing, let the tablet dissolve all the way on your tongue, which will take an average time of 11 seconds (ranging from 2 to 27 seconds).
    - If your dose is more than one tablet of SPRITAM, put only one tablet in your mouth to dissolve at a time. Repeat the step, if needed to take your full dose.
  - How to take SPRITAM with a small amount of liquid in a cup:
    - Add whole SPRITAM tablet or tablets to a small amount of liquid in a cup (1 tablespoon or enough liquid to cover the medicine), and swirl gently.
    - Allow the tablet or tablets to fully break apart (disperse) in the liquid. Then swallow all of the medicine mixture by mouth right away using the cup or an oral syringe.
    - If there is any SPRITAM mixture left in the cup, add a small amount of liquid to the cup, swirl gently, and swallow the remaining medicine mixture by mouth using the cup or oral syringe.
  - How to give SPRITAM using a Nasogastric Tube (NG Tube) or Gastrostomy Tube (G-Tube):
    - Your healthcare provider will tell you the right size of tube to use to give SPRITAM.
    - Place the number of whole tablets needed for the prescribed dose in a small dosing cup. Do not use partial tablets.
    - Add about 10 mL (2 teaspoonfuls) of room temperature water into the small dosing cup.
    - Gently swirl the cup until the tablet or tablets break apart in the liquid.
    - Place a 10 mL oral catheter-tip syringe in the medicine mixture.
    - Pull up on the syringe plunger to withdraw all the medicine mixture from the cup into the syringe.
    - Hold the syringe in an up and down (vertical) position and attach it to the feeding tube. Push the plunger to give the medicine mixture right away through the feeding tube.
    - Remove the empty syringe from the feeding tube.
    After giving SPRITAM through a feeding tube, flush the feeding tube 2 times as follows to make sure the full dose is given:
    - Add another 10 mL of room temperature water in the dosing cup that contained the medicine mixture.
    - Swirl the cup to mix any remaining medicine.
    - Place the same 10 mL syringe into the remaining medicine mixture and pull up on the syringe plunger to withdraw all the medicine mixture.
    - Right away, attach the syringe to the feeding tube and push the plunger to flush the feeding tube.
- SPRITAM can be taken with or without food.
- If you take too much SPRITAM, call your Poison Control Center at 1-800-222-1222 or go to the nearest emergency room right away.

What should I avoid while taking SPRITAM?

Do not drive, operate machinery or do other dangerous activities until you know how SPRITAM affects you. SPRITAM may make you dizzy or sleepy.

What are the possible side effects of SPRITAM?

SPRITAM can cause serious side effects. See "What is the most important information I should know about SPRITAM?"
Call your healthcare provider right away if you have any of these symptoms:

- mood and behavior changes such as aggression, agitation, anger, anxiety, apathy, mood swings, depression, hostility, and irritability. A few people may get psychotic symptoms such as hallucinations (seeing or hearing things that are really not there), delusions (false or strange thoughts or beliefs), and unusual behavior.
- extreme sleepiness, tiredness, and weakness.
- allergic reactions such as swelling of the face, lips, eyes, tongue, and throat, trouble swallowing or breathing, and hives.
- a skin rash. Serious skin rashes can happen after you start taking SPRITAM. There is no way to tell if a mild rash will become a serious reaction. Call your healthcare provider right away if you get a rash while taking SPRITAM.
- a serious allergic reaction that may affect your skin or other parts of your body such as your liver, kidneys, heart, or blood cells. This allergic reaction can be life-threatening and can cause death, particularly if it is not treated as early as possible. Call your healthcare provider right away if you have:
  - a skin rash
  - swelling of your face
  - dark urine
  - fever or swollen glands that do not go away
  - shortness of breath
  - yellowing of the skin or whites of the eyes
- problems with muscle coordination (problems walking and moving).

The most common side effects seen in adults who take SPRITAM include:

- sleepiness
- infection
- weakness
- dizziness

The most common side effects seen in children who take SPRITAM include the side effects above and:

- tiredness
- decreased appetite
- irritability
- acting aggressive
- nasal congestion

Tell your healthcare provider if you have any side effect that bothers you or that does not go away.

These are not all the possible side effects of SPRITAM. For more information, ask your healthcare provider or pharmacist.

Call your doctor for medical advice about side effects. You may report side effects to FDA at 1-800-FDA-1088. You may also report side effects to Aprecia Pharmaceuticals, LLC at 1-844-882-7732.

How should I store SPRITAM?

- Store SPRITAM at room temperature, between 59°F to 86°F (15°C to 30°C).
- Keep SPRITAM and all medicines out of the reach of children.

General information about the safe and effective use of SPRITAM.

Medicines are sometimes prescribed for purposes other than those listed in a Medication Guide. Do not use SPRITAM for a condition for which it was not prescribed. Do not give SPRITAM to other people, even if they have the same symptoms that you have. It may harm them. You can ask your pharmacist or healthcare provider for information about SPRITAM that is written for health professionals. You can also get information about SPRITAM at 1-844-882-7732.

What are the ingredients in SPRITAM?

Active ingredient: levetiracetam

Inactive ingredients: colloidal silicon dioxide, glycerin, mannitol, microcrystalline cellulose, polysorbate 20, povidone, sucralose, butylated hydroxyanisole, and natural and artificial spearmint flavor.

Manufactured by Aprecia Pharmaceuticals, LLC, Mason, OH 45040 USA

Distributed by Prasco, LLC, Mason, OH 45040 USA

SPRITAM® is a registered trademark of Aprecia Pharmaceuticals, LLC.

Patent(s): www.aprecia.com/patents

©2025 Aprecia Pharmaceuticals, LLC all rights reserved. Printed in the USA

This Medication Guide has been approved by the U.S Food and Drug Administration.
LB-PG-0001.R

Revised: 7/2025

PACKAGE LABEL

PRINCIPAL DISPLAY PANEL - NDC: 43485-101-60 - 250 mg Carton Label

PACKAGE LABEL

PRINCIPAL DISPLAY PANEL - NDC: 43485-102-60 - 500 mg Carton Label

PACKAGE LABEL

PRINCIPAL DISPLAY PANEL - NDC: 43485-101-03 - 250 mg Carton Label

PACKAGE LABEL

PRINCIPAL DISPLAY PANEL - NDC: 43485-102-03 - 500 mg Carton Label